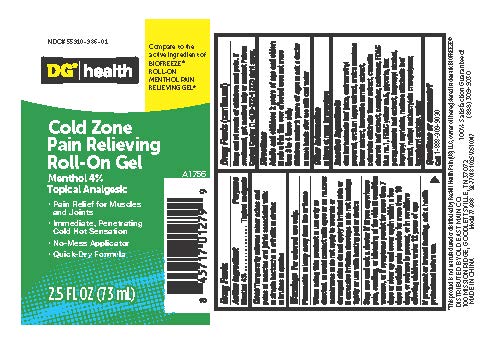 DRUG LABEL: Dollar General Menthol Pain Relief Gel Rollon
NDC: 55910-986 | Form: GEL
Manufacturer: Dolgencorp, LLC
Category: otc | Type: HUMAN OTC DRUG LABEL
Date: 20251016

ACTIVE INGREDIENTS: MENTHOL 4 g/1 mL
INACTIVE INGREDIENTS: WATER; CARBOMER 940; CAMPHOR (NATURAL); AMINOMETHYL PROPANOL; ISOPROPYL ALCOHOL; ARNICA MONTANA FLOWER; GLYCERIN; ISOPROPYL MYRISTATE; CALENDULA OFFICINALIS FLOWER; .ALPHA.-TOCOPHEROL ACETATE; MELISSA OFFICINALIS LEAF; ALOE BARBADENSIS LEAF; ARCTIUM LAPPA WHOLE; CAMELLIA SINENSIS LEAF; ILEX PARAGUARIENSIS LEAF; BOSWELLIA SERRATA GUM; METHYL METHACRYLATE/GLYCOL DIMETHACRYLATE CROSSPOLYMER; FD&C YELLOW NO. 5; FD&C BLUE NO. 1

Dollar General Menthol Pain Relief Gel

Active Ingredient

Menthol 4%

Purpose

Topical analgesic

Uses

Temporarily relieves minor aches and pains of muscles and joints associated with:

■ simple backache

■arthritis

■strains

■bruises

■sprains

Warnings

For external use only

Flammable

- keep away from fire or flame

When using this product

■ use only as directed.

■avoid contact with eyes or on mucous membranes

■do not apply to woundsor damaged skin

■do not apply to irritated skin or if excessive irritation develops

■do not bandage tightly or use with heating pad or device

Stop use and ask a doctor if

■ you experience pain, swelling, or blistering of the skin

■condition worsens, or if symptoms persist for more than 7 days or clear up and occur againwithin a few days

■arthritic pain persists for more than 1O days, or redness is present, or in conditions affecting children under 12 years of age

If pregnant or breast feeding

ask a health professional before use.

Keep out of reach of children and pets.

If swallowed,get medical help or contact Poison Control Center (1-800-222-1222) right away.

Directions

Adults and children 2 years of age and older:

■ ruba thin film over affected area not more than 3 to 4 times daily

Children under 2 years of age:

■ask a doctor

■ wash hands after use with cool water

Other information

Store at room temperature

Inactive Ingredients

aloe barbadensis leaf juice, amin□methyl propanol, arctium lappa extract, arnica montana flower extract, boswellia serrata extract, calendula officinalis flower extract, camellia sinensis leaf extract, camphor,carbomer,FO&C blue no.1,FD&C yellow no.5,glycerin,ilex paraguariensis leaf
extract, isapropyl alcohol, isapropyl myristate, melissa officinalisleaf extract, methyl methacrylate crosspolymer, tocopheryl acetate, water